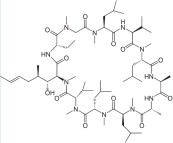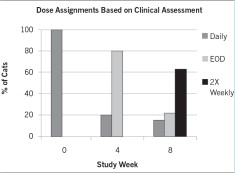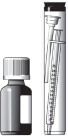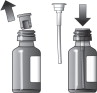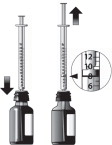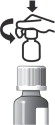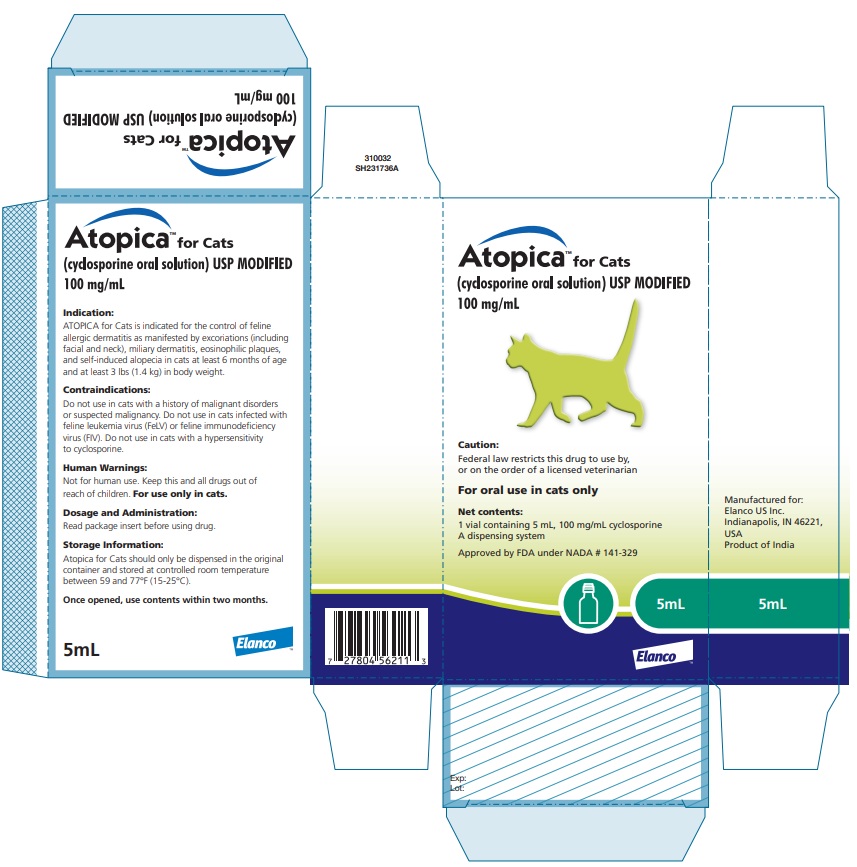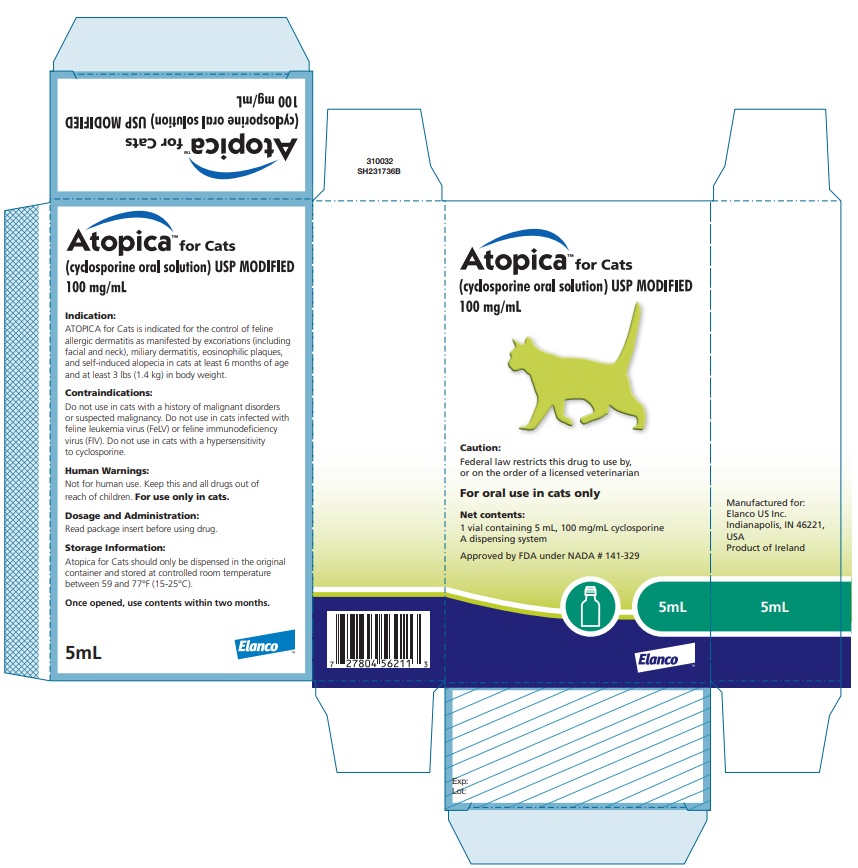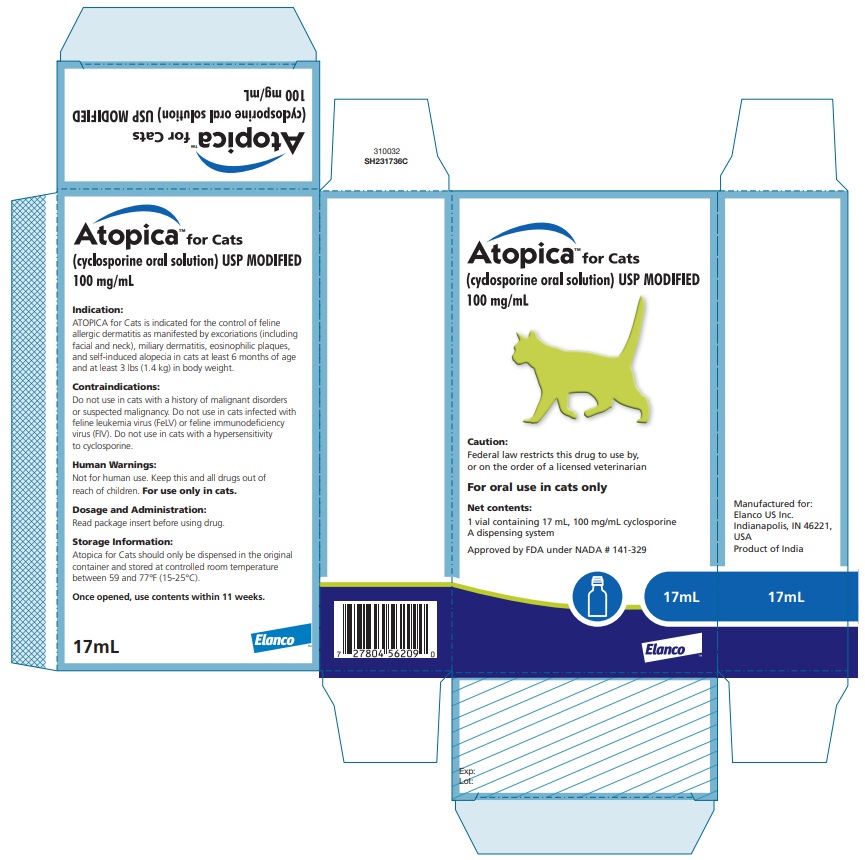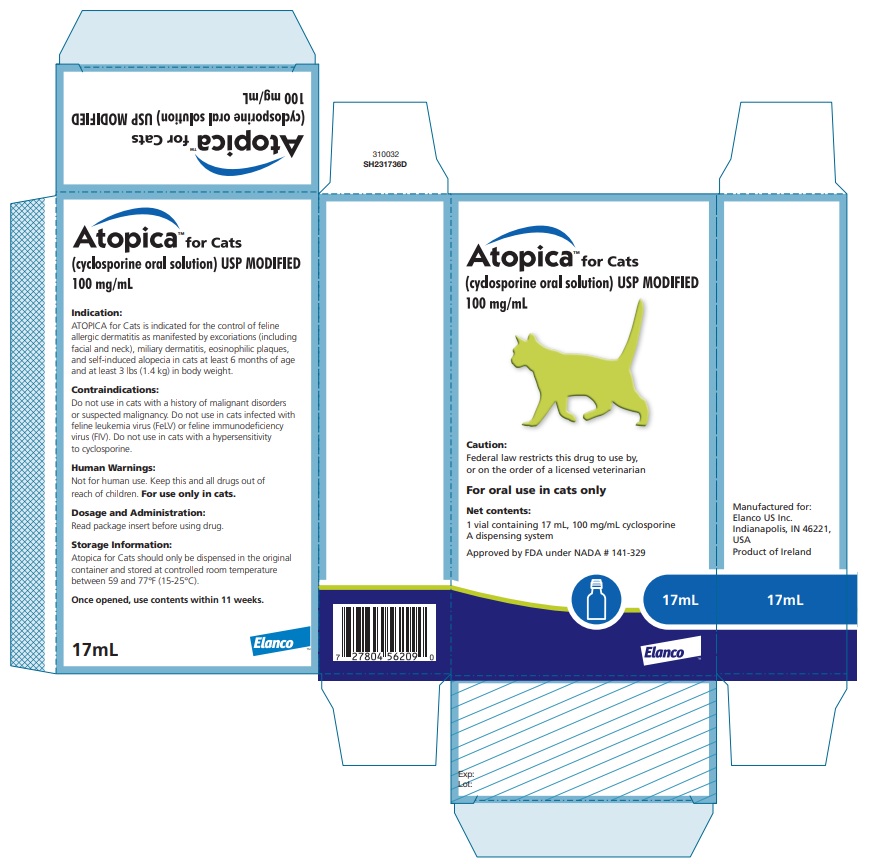 DRUG LABEL: Atopica for Cats
NDC: 58198-9725 | Form: SOLUTION
Manufacturer: Elanco US Inc.
Category: animal | Type: PRESCRIPTION ANIMAL DRUG LABEL
Date: 20260115

ACTIVE INGREDIENTS: cyclosporine 100 mg/1 mL

Atopica™ for Cats
(cyclosporine oral solution) USP MODIFIED
100 mg/mL

Caution:

Federal Law restricts this drug to use by or on the order of a licensed veterinarian.

Description:

ATOPICA for Cats (cyclosporine oral solution) USP MODIFIED is an oral formulation of cyclosporine that immediately forms a microemulsion in an aqueous environment. Cyclosporine, the active ingredient in ATOPICA for Cats, is a cyclic polypeptide, immune modulating agent consisting of 11 amino acids. It is produced as a metabolite by the fungal species Beauveria nivea.

Chemically, cyclosporine A is designated Cyclo[[(E)(2S,3R,4R)-3-hydroxy-4-methyl-2-(methylamino)-6-octenoyl]-L-2-aminobutyryl-N-methylglycyl-N-methyl-L-leucyl-L-valyl-N-methyl-L-leucyl-L-alanyl-D-ananyl-N-methyl-L-leucyl-N-methyl-L-leucyl-N-methyl-L-valyl].

The structural formula is:

Indication:

ATOPICA for Cats is indicated for the control of feline allergic dermatitis as manifested by excoriations (including facial and neck), miliary dermatitis, eosinophilic plaques, and self-induced alopecia in cats at least 6 months of age and at least 3 lbs (1.4 kg) in body weight.

Dosage and Administration:

Always provide the Instructions for Assembling the Dispensing System and Preparing a Dose of ATOPICA for Cats and the Information for Cat Owners with prescription.

The initial dose of ATOPICA for Cats is 3.2 mg/lb/day (7 mg/kg/day) as a single daily dose for a minimum of 4 to 6 weeks or until resolution of clinical signs. Following this initial daily treatment period, the dose of ATOPICA for Cats may be tapered by decreasing the frequency of dosing to every other day or twice weekly to maintain the desired therapeutic effect. ATOPICA for Cats should be administered directly on a small amount of food or orally just after feeding. Whenever possible, ATOPICA for Cats should be administered on a consistent schedule with regard to meals and time of day. If a dose is missed, the next dose should be administered (without doubling) as soon as possible, but dosing should be no more frequent than once daily.

The dispensing system includes an oral dosing syringe graduated in 1 lb increments. To dose the cat, the syringe should be filled to the nearest 1 lb corresponding to the cat's body weight (round down if 0.1 to 0.4 lb, round up if 0.5 to 0.9 lb). Each pound graduation on the syringe delivers a volume of 0.032 mL providing 3.2 mg/lb. Do not rinse or clean the oral dosing syringe between uses. (See Instructions for Assembling the Dispensing System and Preparing a Dose of ATOPICA for Cats)

Contraindications:

Do not use in cats with a history of malignant disorders or suspected malignancy.

Do not use in cats infected with feline leukemia virus (FeLV) or feline immunodeficiency virus (FIV).

Do not use in cats with a hypersensitivity to cyclosporine.

Warnings:

ATOPICA for Cats is a systemic immunosuppressant that may increase the susceptibility to infection and the development of neoplasia. One of 205 field study cats died of the effusive form of feline infectious peritonitis. (See Adverse Reactions)

Persistent, progressive weight loss that resulted in hepatic lipidosis occurred in 2 of 205 cats on treatment with ATOPICA for Cats in field studies. Monitoring of body weight is recommended. (See Adverse Reactions)

Human Warnings:

Not for human use. Keep this and all drugs out of reach of children. For use only in cats.

Special precautions to be taken when administering ATOPICA for Cats:

Do not eat, drink, smoke, or use smokeless tobacco while handling ATOPICA for Cats.

Wash hands after administration.

In case of accidental ingestion, seek medical advice immediately and provide the package insert or the label to the physician.

People with known hypersensitivity to cyclosporine should avoid contact with ATOPICA for Cats.

Precautions:

The safety and effectiveness of ATOPICA for Cats has not been established in cats less than 6 months of age or less than 3 lbs (1.4 kg) body weight.

ATOPICA for Cats is not for use in breeding cats, pregnant or lactating queens.

Cats should be tested and found to be negative for FeLV and FIV infections before treatment.

As with any immunosuppressive regimen, exacerbation of sub-clinical neoplastic and infectious conditions may occur. ATOPICA for Cats is not for use with other immunosuppressive agents.

Cats that are seronegative for Toxoplasma gondii may be at risk of developing clinical toxoplasmosis if they become infected while under treatment, which can be fatal. In a controlled laboratory study, cats seronegative for T. gondii were administered cyclosporine and subsequently infected with T. gondii, resulting in increased susceptibility to infection and subsequent expression of toxoplasmosis.

Cyclosporine did not increase T. gondii oocyst shedding (see Animal Safety). Potential exposure of seronegative cats to T. gondii should be avoided (e.g. keep indoors, avoid raw meat or scavenging).

In cases of clinical toxoplasmosis or other serious systemic illness, stop treatment with cyclosporine and initiate appropriate therapy.

ATOPICA for Cats may cause elevated levels of serum glucose, creatinine, and urea nitrogen. ATOPICA for Cats should be used with caution in cases with diabetes mellitus or renal insufficiency.

ATOPICA for Cats should be used with caution with drugs that affect the P-450 enzyme system. Simultaneous administration of ATOPICA for Cats with drugs that suppress the P-450 enzyme system, such as azoles (e.g. ketoconazole), may lead to increased plasma levels of cyclosporine.

Treatment with ATOPICA for Cats may result in decreased immune response to vaccination. Naïve cats may not develop protective titers during treatment (see Animal Safety).

Adverse Reactions:

The clinical safety of ATOPICA for Cats was assessed in a masked, controlled 6-week field study followed by a 12-week open-labeled dose-tapering field study. In these two field studies, 205 cats received treatment with ATOPICA for Cats for up to 126 days.

Two cats died or were euthanized within two weeks following study exit. One cat was diagnosed with the effusive form of feline infectious peritonitis and died following normal study exit, and one cat with pre-existing anemia that worsened during the study was diagnosed with aplastic anemia and euthanized because of a poor prognosis for recovery.

Fourteen of the 205 cats (6.8%) were withdrawn from the studies due to the occurrence of an adverse reaction. Adverse reactions in these 14 cats included weight loss, anorexia, vomiting, diarrhea, hypersalivation, lethargy, hepatic lipidosis and jaundice, upper respiratory signs, ocular discharge, cough, toxoplasmosis, lymphopenia, anemia, bacterial dermatitis, seizure, ataxia, and small cell gastrointestinal lymphoma.

The most commonly reported adverse reaction was vomiting. In most cases, vomiting spontaneously resolved with continued dosing. Adverse reactions occurred most often with daily dosing compared to other dosing regimes.

Adverse reactions reported with greater than 2% frequency in the two field studies.

Adverse Reaction* | Number (Percent) of Cases n = 205
Vomiting/Retching/Regurgitation | 72 (35.1%)
Weight Loss | 42 (20.5%)
Diarrhea | 31 (15.1%)
Anorexia/Decreased Appetite | 29 (14.1%)
Lethargy/Malaise | 28 (13.6%)
Hypersalivation | 23 (11.2%)
Behavioral Disorder (hiding, hyperactivity, aggression) | 18 (8.8%)
Ocular Discharge/Epiphora/Conjunctivitis | 14 (6.8%)
Sneezing/Rhinitis | 11 (5.4%)
Gingivitis/Gingival Hyperplasia | 9 (4.4%)
Polydipsia | 6 (2.9%)
*Cats may have experienced more than one type or occurrence of a reaction during the studies.

The following adverse reactions were reported in less than or equal to 2% of cats treated with ATOPICA for Cats in the two field studies: bacterial dermatitis, hepatic lipidosis and jaundice, gastrointestinal small cell lymphoma, constipation, cough, toxoplasmosis, muscle wasting, muscle tremors, ataxia, convulsion, polyuria, urinary tract infection, inappropriate urination or defection, seborrhea, worsening otitis externa, papilloma, leukotrichia (whitening of hair) and excessive hair growth, anemia, lymphopenia, worsening monocytosis, worsening neutrophilia, hyperglobulinemia, increased serum creatinine and urea nitrogen, and increased alanine aminotransferase.

Contact Information:

To report suspected adverse drug events or for technical assistance, contact Elanco US Inc. at 1-888-545-5973. For additional information about adverse drug experience reporting for animal drugs, contact FDA at 1-888-FDA-VETS or http://www.fda.gov/reportanimalae

Information for Cat Owners:

Owners should be advised to discontinue ATOPICA for Cats and contact their veterinarian in case of signs of serious illness and/or persistent, progressive weight loss. Owners should be informed of the risks of increased susceptibility to infection and the development of neoplasia, and they should be provided advice on how to avoid exposure of their cat to Toxoplasma gondii infection.

Clinical Pharmacology:

Cyclosporine is an immunosuppressive agent that has been shown to work via suppression of T-helper and T-suppressor cells and inhibition of interleukin-2. It does not depress hematopoesis or the function of phagocytic cells. ATOPICA for Cats is not a corticosteroid or antihistamine.

Following an intravenous dose of 2 mg/kg in a 24-hour fasted state, clearance of cyclosporine A in cats was 0.199 L/kg x h and half life was ~24 hours. After oral administration, the terminal elimination half life has been estimated to be as short as 6.8 to longer than 40 hours in some normal healthy cats.

The bioavailability of ATOPICA for Cats is highly variable both within and between cats. A pharmacokinetic study showed no consistent difference in the mean extent of drug absorption when administered orally to fed or fasted cats or mixed in with food.

Blood levels of cyclosporine in field studies were highly variable, even among cats with similar clinical response, suggesting no generalizable correlations can be made between cats with regard to blood cyclosporine levels and clinical response (effectiveness and safety). Nevertheless, individual differences in the relationship between drug exposure and clinical response may exist. Therefore, to minimize individual fluctuations in drug absorption, ATOPICA for Cats should be administered on a consistent schedule with regard to meals and time of day.

Effectiveness:

A masked, controlled field study was conducted at 24 sites from various geographic locations in the United States and Canada. In this study, 217 client-owned cats with clinical signs consistent with allergic dermatitis (miliary dermatitis, excoriations including facial or neck, self-induced alopecia and eosinophilic plaques) along with non-seasonal localized or generalized pruritus, were randomly assigned in a 2:1 ratio and received either ATOPICA for Cats or a control solution (the excipients of ATOPICA for Cats without the cyclosporine). Owners administered treatment in a small amount of food or directly in the cat's mouth just after feeding once daily for up to 6 weeks. No additional therapy with antihistamines, corticosteroids or medicated shampoos was permitted.

Effectiveness was evaluated in 181 cats. Cats in the ATOPICA for Cats treatment group had a 65.1% reduction in mean total lesion score, compared to cats in the control treatment group, which had a 9.2% reduction in mean total lesion score. The percent of cats identified as treatment success by the Owner was 78.6% in the ATOPICA for Cats group compared to 26.2% in the control group. Compared to the control group, the ATOPICA for Cats group had improved mean ratings for Investigator assessment of overall improvement, Owner and Investigator assessment of pruritus, and number of body regions with lesions.

After drop-out from or completion of the masked 6-week field study, 191 cats were enrolled in a 12-week open-labeled field study to evaluate dose tapering of ATOPICA for Cats. The graph below shows the dose assignments for each 4-week dosing period. At study entry, all cats were assigned daily doses. At Week 4, cats were assigned daily or every other day (EOD) dosing, based on clinical improvement. At Week 8, cats were assigned daily, EOD, or twice weekly (2X Weekly) dosing for the final month of the study. Cats with poor responses exited the study at Weeks 4 and 8. At study exit at Week 12, 62.9%, 21.6%, and 15.5% of the remaining 97 evaluable cats were on twice weekly, EOD, and daily dosage regimens, respectively.

ATOPICA for Cats was used in conjunction with various medications including a macrocyclic lactone and other antiparasitic agents, systemic antimicrobials, and topical skin and otic cleansers and antimicrobials.

Animal Safety:

In a 6-month safety study, forty (20 male and 20 female) 6-month old cats were randomized into 5 treatment groups and administered 0, 8, 16, 24 or 40 mg/kg/day ATOPICA for Cats (0, 1, 2, 3 or 5X the maximum therapeutic dose). An intermittent interventricular conduction disturbance was noted on electrocardiogram in one 3X and one 5X treatment group cat following 6 months of dosing. A 5X cat was euthanized after two weeks of treatment following a rapidly-declining clinical condition including recumbency, inappetance, dehydration, and decreased body weight. A post-mortem examination showed a healing rib fracture and bone marrow hypocellularity characterized by a moderate reduction in the number of bone marrow cells from multiple lineages. Hematology parameters drawn prior to euthanasia for this cat did not reveal abnormalities indicative of bone marrow hypocellularity. A 5X female cat presented with abdominal fibroadenomatous nodules during the study. Lymphoma of the kidneys and a mesenteric lymph node were present on necropsy in one 5X male, which is likely related to the immunosuppressive effects of cyclosporine treatment. Activated partial thromboplastin time (APTT) was prolonged in treated cats when compared to control cats.

A safety study was conducted to evaluate the effect of ATOPICA for Cats on the development of vaccine titers following vaccination in cats. Thirty-two cats (16 males and 16 females) were randomized into two treatment groups. Group 1 cats served as the control group and were sham dosed. Group 2 cats were administered ATOPICA for Cats at a dose of 24 mg/kg (3X the maximum therapeutic dose) orally once daily for 56 days. All cats were approximately 7 months of age at the start of the study and previously vaccinated against feline calici virus (FCV), feline panleukopenia virus (FPV), feline leukemia virus (FeLV), feline herpes virus-1 (FHV-1) and rabies with the final pre-treatment vaccines administered 16 weeks prior to treatment with cyclosporine. Cats were naïve to the feline immunodeficiency virus (FIV) vaccine, which was administered after 28 days on cyclosporine. After booster vaccinations on Day 28, titers for FCV, FPV, FeLV, FHV-1 and rabies were decreased in cyclosporine treated cats compared to control cats, but these titers remained adequate in both treatment groups. In contrast, cats on high-dose cyclosporine failed to develop titers to the novel vaccine (FIV). An increase in incidence and frequency of diarrhea, vomiting, and salivation were noted in Group 2 cats. One female cat treated with cyclosporine was observed to be in estrus during the study compared to 5 of the female control cats. One cat treated with cyclosporine was noted as having a slow or absent startle reflex, displayed ataxia, had small lymph nodes, thin body condition, and gas and fluid filled loops of intestine. Lymphocyte counts were lower in treated cats when compared to control. APTT was prolonged in treated cats when compared to control cats. Cholesterol, glucose, total protein, blood urea nitrogen, and creatinine values were elevated in cyclosporine treated cats with values just above the normal reference range. Glucosuria was noted in three treated animals that also had hyperglycemia.

A safety study was conducted to evaluate the effects of ATOPICA for Cats on the clinical course of Toxoplasma gondii. Thirty domestic short-haired cats (15 males and 15 females) ranging in age from 1-2 years were randomized into three treatment groups. Group 1 cats served as the control group and were administered placebo. Group 2 cats were administered placebo for 84 days followed by treatment with ATOPICA for Cats for 42 days. Group 3 cats were treated with ATOPICA for Cats for 126 days. ATOPICA for Cats was administered at a target dose of 7.5 mg/kg orally once daily. All cats were infected with T. gondii cysts on Study Day 42. One cat was found dead and another was euthanized (both in Group 3) within six weeks following infection due to complications related to toxoplasmosis. Clinical signs typical of T. gondii infection, including bloody feces, lethargy, and vomiting/regurgitation, were also seen in most of the remaining cats, but resolved within six weeks following infection. Decreases in body weight and food consumption were seen in some cats from each group, but these changes were reversible as the animals recovered from clinical toxoplasmosis. APTT was prolonged in Group 2 and 3 cats receiving cyclosporine when compared to Group 1 cats. Cholesterol, glucose and total protein/globulin values were elevated in cyclosporine treated cats. Ocular changes consistent with toxoplasmosis were seen in one to two cats in each group. The oocyst shedding period and number of oocysts shed were increased in Group 1 and 2 cats compared to Group 3 cats. All inoculated cats developed T. gondii IgG antibodies; IgM titers were detected in only 3 cats. Post-mortem examinations revealed mild to moderate inflammation in the central nervous system and pulmonary tissues, with the highest incidence and severity generally following this trend: Group 3 > Group 2 > Group 1. Lesions were consistent with T. gondii infection and were more prevalent in males than females. T. gondii organisms were only detected histopathologically in the tissues of the two Group 3 cats that died of toxoplasmosis.

Storage Information:

ATOPICA for Cats should only be dispensed in the original container and stored at controlled room temperature between 59 and 77°F (15-25°C). Once opened, use contents within two months for the 5 mL container and 11 weeks for the 17 mL container.

How Supplied:

ATOPICA for Cats (cyclosporine oral solution) USP MODIFIED is supplied in glass amber bottles of 5 and 17 mL at 100 mg/mL. A dispensing system is included (See Instructions for Assembling the Dispensing System and Preparing a Dose of ATOPICA for Cats).

Manufactured for:
Elanco US Inc. Indianapolis, IN 46221, USA
Product of Ireland
Product of India
Approved by FDA under NADA # 141-329
Revision Date: November 2025
Atopica, Elanco and the diagonal bar logo are trademarks of Elanco or its affiliates.
© 2025 Elanco or its affiliates

Instructions for Assembling the Dispensing System and Preparing a Dose of ATOPICA™ for Cats (cyclosporine oral solution) USP MODIFIED

Assembling the Dispensing System

The dispensing system consists of 4 parts:

1. A bottle containing the medicine, with rubber stopper and a screw cap to close the bottle after use.
2. A plastic adapter with dip tube that you will push into the neck of the bottle. The adapter must always remain in the bottle after first use.
3. An oral dosing syringe that fits into the top of the plastic adapter to withdraw the prescribed dose of medicine from the bottle.
4. A plastic vial containing the plastic adapter and oral dosing syringe. Save the plastic vial to store the oral dosing syringe between each use.

Fitting the Plastic Adapter into the New Bottle of Medicine

- Remove and save the screw cap.
- Remove and dispose of the rubber stopper.
- Hold the open bottle upright on a table and push the plastic adapter firmly into the neck of the bottle as far as you can, then close the bottle with the screw cap.
- To provide a child-resistant closure, push down on the child-resistant screw cap as you turn it.

Note: To prepare a dose, carefully follow the instructions for Preparing a Dose of Medicine.

Preparing a Dose of Medicine

1. Push and turn the child-resistant screw cap to open the bottle. Note: Always close the bottle with the child-resistant screw cap after use.
2. Check that the plunger of the oral dosing syringe is pushed all the way down.
3. Keep the bottle upright and insert the oral dosing syringe firmly into the plastic adapter.
4. Slowly pull the plunger up so that the oral dosing syringe fills with the medicine.
5. Expel any large bubbles by pushing and pulling the plunger a few times. The presence of a few tiny bubbles is not important for dosing accuracy.
6. Withdraw the dose of medicine prescribed by your veterinarian. The scale on the oral dosing syringe corresponds to the cat's body weight.

Note: If the prescribed dose is more than the maximum volume marked on the oral dosing syringe, you will need to reload the syringe to withdraw the full dose.

7. Remove the oral dosing syringe by gently twisting it out of the plastic adapter.

You can now place the oral dosing syringe over a small amount of food or introduce the syringe in the mouth of your cat and push the medicine out of the syringe. See Information for Cat Owners for complete administration instructions.

Do not rinse or clean the oral dosing syringe between uses. Store the oral dosing syringe in the plastic tube between each use.

ATOPICA for Cats should be stored in the original container at room temperature between 59 and 77°F. Once opened, use contents within two months for the 5 mL container and 11 weeks for the 17 mL container.

Close the bottle with the child-resistant screw cap after use.

Keep out of reach of children!

Always close the bottle with the child-resistant screw cap after use. To provide a child-resistant closure, push down on the child-resistant screw cap as you turn it.

ATOPICA™ for Cats (cyclosporine oral solution) USP MODIFIED Information for Cat Owners

ATOPICA for Cats is indicated for the control of feline allergic dermatitis. Cats with allergic dermatitis scratch, lick and chew their skin which can cause red, raised crusty bumps, open sores and/or hair loss.

Allergic dermatitis is a common skin disease in cats and is caused by allergens such as house dust mites or pollens which stimulate an exaggerated immune response. The disease is chronic, recurrent, and requires lifelong management.

This summary contains important information about ATOPICA for Cats. You should read this information before starting your cat on ATOPICA for Cats. This sheet is provided only as a summary and does not take the place of instructions from your veterinarian. Talk to your veterinarian if you do not understand any of this information or you want to know more about ATOPICA for Cats.

What is ATOPICA for Cats?

ATOPICA for Cats is an oral solution of cyclosporine that lowers the immune response. ATOPICA for Cats selectively acts on the immune cells involved in the allergic reaction. ATOPICA for Cats reduces the inflammation and itching associated with allergic dermatitis.

What kind of results can I expect when my cat takes ATOPICA for Cats for the control of feline allergic dermatitis?

ATOPICA for Cats should be given daily until improvement is seen. This will generally be the case within 4-6 weeks. You should contact your veterinarian if you are not satisfied with your cat's response. Once the signs of allergic dermatitis are satisfactorily controlled, your veterinarian may reduce the frequency of administration of the product. Dose adjustment should only be carried out in consultation with your veterinarian.

Your veterinarian will perform a clinical assessment at regular intervals and adjust the frequency of administration up or down according to the clinical response obtained.

What cats should not take ATOPICA for Cats?

Your cat should not be given ATOPICA for Cats if s/he:

- Has a history of cancer or may possibly have cancer currently
- Has been diagnosed with feline leukemia virus (FeLV) or feline immunodeficiency virus (FIV)
- Is hypersensitive to cyclosporine

What to discuss with your veterinarian before giving ATOPICA for Cats to your cat.

Tell your veterinarian about:

- Any digestive upset (vomiting or diarrhea) your cat has had
- Any history of lack of appetite and/or weight loss your cat has had
- Any serious disease or health conditions your cat has had
- Any allergies that your cat has now or has had
- All medications that you are giving your cat or plan to give your cat, including those you can get without prescription (over the counter) and any dietary supplements
- If you plan to breed your cat, or if your cat is pregnant or nursing

Talk to your veterinarian about:

- What tests might be done before ATOPICA for Cats is prescribed
- The potential side effects your cat may experience while taking ATOPICA for Cats
- How often your cat may need to be examined by your veterinarian
- The risks and benefits of using ATOPICA for Cats

What are the possible side effects that may occur in my cat during therapy with ATOPICA for Cats?

ATOPICA for Cats, like all other drugs, may cause some side effects in individual cats. These are normally mild, but serious side effects have been reported in cats taking ATOPICA for Cats. Serious side effects can, in rare situations, result in death. It is important to stop the medication and contact your veterinarian immediately if you think your cat may have a medical problem or side effect while on ATOPICA for Cats. To report adverse effects, access medical information, or obtain additional product information call 1-888-545-5973.

In clinical studies, the most commonly reported side effect was vomiting. In most cases, the vomiting stopped with continued use. Weight loss, diarrhea, decreased appetite, lethargy, and drooling were the next most frequent side effects observed.

Persistent, progressive weight loss may be associated with more serious side effects. You should monitor your cat's appetite and body weight. If you think that your cat is losing weight, you should contact your veterinarian.

ATOPICA for Cats may increase susceptibility to infection and to the development of tumors.

ATOPICA for Cats should only be given to cats.

People should not take ATOPICA for Cats. Keep ATOPICA for Cats and all medication out of reach of children. Call your physician immediately if you accidentally swallow ATOPICA for Cats.

How to give ATOPICA for Cats to your cat.

ATOPICA for Cats should be given according to your veterinarian's instructions. Your veterinarian will tell you what amount of ATOPICA for Cats is right for your cat. ATOPICA for Cats can be given either mixed with food or directly into the cat's mouth. If given with food, the solution should be mixed with a small amount of food, preferably after a sufficient period of fasting to ensure your cat eats it completely. When given directly into the mouth, insert the oral dosing syringe into the cat's mouth and deliver the entire dose, just after feeding. Whenever possible, you should administer ATOPICA for Cats on a consistent schedule with regard to meals and time of day. Do not change the way you give ATOPICA for Cats to your cat without first speaking with your veterinarian. If a dose is missed, the next dose should be administered (without doubling) as soon as possible, but dosing should be no more frequent than once daily. Do not rinse or clean the oral dosing syringe between uses.

Advice on Correct Administration.

See Instructions for Assembling the Dispensing System and Preparing a Dose of ATOPICA for Cats. If your veterinarian has already assembled the dispensing system, skip the instructions for assembling the dispensing system and follow the instructions for preparing a dose of medicine.

How to Store ATOPICA for Cats.

ATOPICA for Cats should be stored in the original container at room temperature between 59 and 77°F. Once opened, use contents within two months for the 5 mL container and 11 weeks for the 17 mL container.

Special precautions to be taken when administering ATOPICA for Cats.

Do not eat, drink, smoke, or use smokeless tobacco while handling ATOPICA for Cats.

Wash hands after administration.

In case of accidental ingestion, seek medical advice immediately and show the package insert or the label to the physician.

People with known hypersensitivity to cyclosporine should avoid contact with ATOPICA for Cats.

Can ATOPICA for Cats be given with other medications?

ATOPICA for Cats should not be given with other drugs that may lower the immune response.

ATOPICA for Cats has been safely used in conjunction with other common medications. However, interactions with certain medications are possible. Therefore, always tell your veterinarian about all medications that you have given your cat in the past and all medications that you are planning to give with ATOPICA for Cats.

What can I do in case my cat gets more than the prescribed amount of ATOPICA for Cats?

Contact your veterinarian immediately if your cat gets more than the prescribed amount of ATOPICA for Cats.

What else should I know about ATOPICA for Cats?

Toxoplasma gondii is a protozoal parasite that cats can become infected with from eating raw meat. Infection may lead to serious illness (clinical toxoplasmosis). Cats that have not been exposed to Toxoplasma gondii may be at risk of developing clinical toxoplasmosis if they become infected while under treatment with ATOPICA for Cats, which can be fatal. To avoid infection keep your cat indoors, do not feed raw meat, and do not allow your cat to hunt.

If your cat becomes seriously ill, consult your veterinarian who will recommend the appropriate treatment.

This sheet provides a summary of information about ATOPICA for Cats. If you have any questions or concerns about ATOPICA for Cats or allergic dermatitis in cats, talk to your veterinarian.

As with all prescribed medications, ATOPICA for Cats should only be given to the cat for which it was prescribed. It should be given to your cat only for the condition for which it was prescribed, at the prescribed dose, and as directed by your veterinarian.

PA231736A 310024
PA231736B 310024

ElancoTM

Principal Display Panel - 5 mL Carton Label

Atopica™ for Cats

(cyclosporine oral solution) USP MODIFIED

100 mg/mL

Caution:

Federal law restricts this drug to use by,
or on the order of a licensed veterinarian

For oral use in cats only

Net contents:

1 vial containing 5 mL, 100 mg/mL cyclosporine
A dispensing system

Approved by FDA under NADA # 141-329

5 mL

Elanco™

Principal Display Panel - 17 mL Carton Label

Atopica™ for Cats

(cyclosporine oral solution) USP MODIFIED

100 mg/mL

Caution:

Federal law restricts this drug to use by,
or on the order of a licensed veterinarian

For oral use in cats only

Net contents:

1 vial containing 17 mL, 100 mg/mL cyclosporine
A dispensing system

Approved by FDA under NADA # 141-329

17 mL

Elanco™